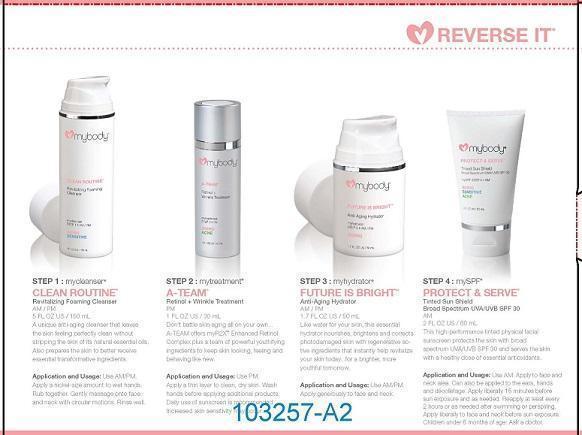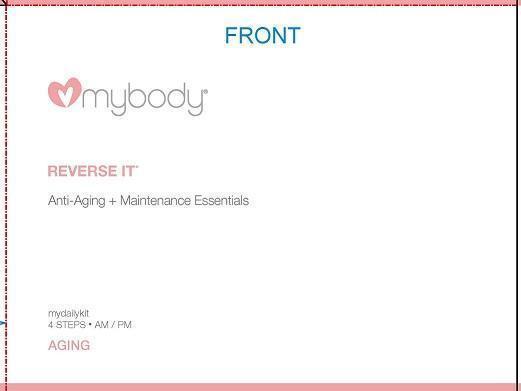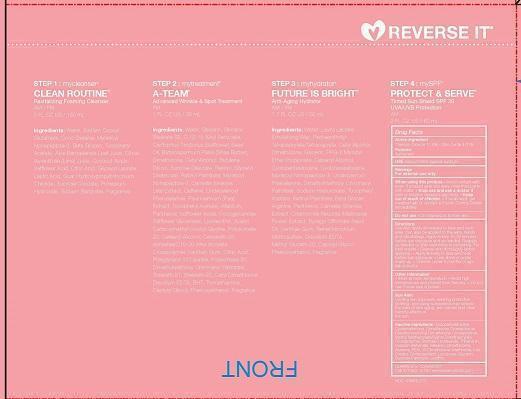 DRUG LABEL: REVERSE IT KIT
NDC: 49520-503 | Form: KIT | Route: TOPICAL
Manufacturer: mybody
Category: otc | Type: HUMAN OTC DRUG LABEL
Date: 20140630

ACTIVE INGREDIENTS: TITANIUM DIOXIDE 11 g/100 mL; ZINC OXIDE 4 g/100 mL
INACTIVE INGREDIENTS: CYCLOMETHICONE 5; CYCLOMETHICONE; DIMETHICONE/VINYL DIMETHICONE CROSSPOLYMER (SOFT PARTICLE); METHYL METHACRYLATE/GLYCOL DIMETHACRYLATE CROSSPOLYMER; SORBITAN ISOSTEARATE; TRIBEHENIN; CALCIUM BEHENATE; MELANIN SYNTHETIC (TYROSINE, PEROXIDE); DIMETHICONOL (41 MPA.S); ALUMINUM OXIDE; PEG-10 DIMETHICONE (600 CST); METHICONE (20 CST); FERRIC OXIDE RED; CHOLECALCIFEROL; LYCOPENE; GLYCERIN; SUCROSE PALMITATE; LECITHIN, SOYBEAN

ACTIVE INGREDIENT

TITANIUM DIOXIDE 10.9%

ZINC OXIDE 4.01%

PURPOSE

SUNSCREEN

INDICATIONS AND USAGE

USE HELPS PROTECT AGAINST SUNBURN

WARNINGS

FOR EXTERNAL USE ONLY

WHEN USING THIS PRODUCT

- AVOID CONTACT WITH EYES. IF PRODUCT GETS INTO EYES, RINSE THOROUGHLY WITH WATER.

- STOP USE AND ASK A DOCTOR IF RASH OR IRRITATION DEVELOPS AND LASTS.

KEEP OUT OF REACH OF CHILDREN. IF SWALLOWED, GET MEDICAL HELP OR CONTACT A POISON CONTROL CENTER RIGHT AWAY.

DO NOT USE

- ON INFLAMED OR BROKEN SKIN.

DIRECTIONS

USE AM. APPLY AS NEEDED TO FACE AND NECK AREA. CAN ALSO BE APPLIED TO THE EARS, HANDS AND DECOLETAGE. APPLY EVENLY 15-30 MINUTES BEFORE SUN EXPOSURE AND AS NEEDED. REAPPLY AS NEEDED OR AFTER SWIMMING OR PERSPIRING. FOR BEST RESULTS

- CLEANSE SKIN THOROUGHLY BEFORE APPLYING.
- APPLY LIBERALLY TO FACE AND NECK BEFORE SUN EXPOSURE.
- USE ALONE OR UNDER MAKE-UP.
- CHILDREN UNDER 6 MONTHS OF AGE, ASK A DOCTOR.

OTHER INFORMATION

- STORE AT ROOM TEMPERATURE
- AVOID HIGH TEMPERATURES AND PROTECT FROM FREEZING.
- DO NOT USE IF INNER SEAL IS BROKEN.

SUN ALERT

LIMITING SUN EXPOSURE, WEARING PRODUCTIVE CLOTHING, AND USING SUNSCREEN MAY REDUCE THE RISKS OF SKIN AGING, SKIN CANCER AND OTHER HARMFUL EFFECTS OF THE SUN.

INACTIVE INGREDIENT

INACTIVE INGREDIENTS: CYCLOPENTASILOXANE, CYCLOMETHICONE, DIMETHICONE CROSSPOLYMER, DIMETHICONE/VINYL DIMETHICONE CROSSPOLYMER, METHYL METHACRYLATE/GLYCOL DIMETHACRYLATE CROSSPOLYMER, SORBITAN ISOSTEARATE, TRIBEHENIN, CALCIUM BEHENATE, MELANIN, DIMETHICONOL, ALUMINA, PEG-10 DIMETHICONE, METHICONE, IRON OXIDES, CHOLECALCIFEROL, LYCOPENE, GLYCERIN, SUCROSE PALMITATE, LECITHIN.

QUESTIONS OR COMMENTS?

CALL 877.423.1314 * WWW.LOVEMYBODY.COM